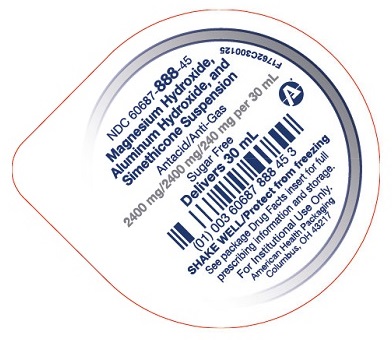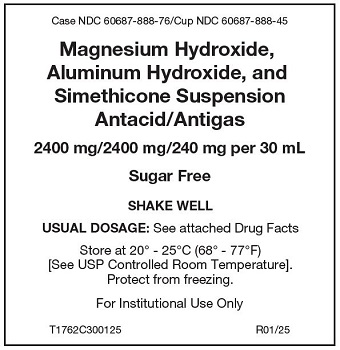 DRUG LABEL: Aluminum Hydroxide, Magnesium Hydroxide, and Dimethicone
NDC: 60687-888 | Form: SUSPENSION
Manufacturer: American Health Packaging
Category: otc | Type: HUMAN OTC DRUG LABEL
Date: 20250715

ACTIVE INGREDIENTS: ALUMINUM HYDROXIDE 400 mg/5 mL; MAGNESIUM HYDROXIDE 400 mg/5 mL; DIMETHICONE, UNSPECIFIED 40 mg/5 mL
INACTIVE INGREDIENTS: BUTYLPARABEN; PROPYLPARABEN; HYPROMELLOSE 2910 (4000 MPA.S); PROPYLENE GLYCOL; SORBITOL; SACCHARIN SODIUM; PEPPERMINT OIL; CYCLOMETHICONE 4; WATER

Magnesium Hydroxide, Aluminum Hydroxide, and Simethicone Suspension

Active ingredients (in each 30 mL cup)

Aluminum hydroxide (equiv. to dried gel, USP) 2400 mg | Antacid
Magnesium hydroxide 2400 mg | Antacid
Simethicone 240 mg | Antigas

Purpose

Antacid/Antigas

Uses

for the relief of:

- acid indigestion
- heartburn
- sour stomach
- upset stomach due to these symptoms
- pressure and bloating commonly referred to as gas

Warnings

Do not take more than 2 unit dose cups (60 mL) in a 24-hour period or use the maximum dosage for more than 2 weeks except under the advice and supervision of a physician.

Ask a doctor before use if you have

- kidney disease
- a magnesium-restricted diet

Ask a doctor or pharmacist before use if you are

- presently taking a prescription drug. Antacids may interact with certain prescription drugs.

Stop use and ask a doctor if

- symptoms last more than 2 weeks.

Directions

- shake well before using
- do not take more than 2 unit dose cups (60 mL) in 24 hours or use the maximum dosage for more than 2 weeks

adults and children 12 years and older | Take 30 mL, one unit dose cup, one to two times daily, or as directed by a doctor.
children under 12 years | consult a physician

Other information

- each 30 mL contains: magnesium 1,002 mg, sodium 13.44 mg
- Store at 20° - 25°C (68° - 77°F) [see USP Controlled Room Temperature].
- protect from freezing
- White colored, cherry flavored liquid supplied in the following oral dosage form:
- 30 mL unit dose cups: 100 cups (10 x 10) NDC 60687‐888‐76

Inactive ingredients

butylparaben, hydroxypropyl methylcellulose, flavoring, propylene glycol, propylparaben, purified water, saccharin sodium, and sorbitol solution.

Questions or comments?

Call 1-800-845-8210

DO NOT USE IF SEAL IS BROKEN.

Distributed by:

American Health Packaging
Columbus, OH 43217

R01/25

Principal Display Panel – Tray Label

Case NDC 60687-888-76/Cup NDC 60687-888-45

Magnesium Hydroxide,
Aluminum Hydroxide, and
Simethicone Suspension
Antacid/Antigas

2400 mg/2400 mg/240 mg per 30 mL

Sugar Free

SHAKE WELL

USUAL DOSAGE: See attached Drug Facts

Store at 20° to 25°C (68° to 77°F)
[See USP Controlled Room Temperature].
Protect from freezing.

For Institutional Use Only

T1762C300125 R01/25

Principal Display Panel – Cup – 2400 mg/2400 mg/240 mg 30 mL

NDC 60687- 888-45

Magnesium Hydroxide,
Aluminum Hydroxide, and
Simethicone Suspension

Antacid/Anti-Gas

2400 mg/2400 mg/240 mg per 30 mL

Sugar Free

Delivers 30 mL

SHAKE WELL/Protect from freezing

See package Drug Facts insert for full
prescribing information and storage.

For Institutional Use Only.

American Health Packaging
Columbus, OH 43217

F1762C300125